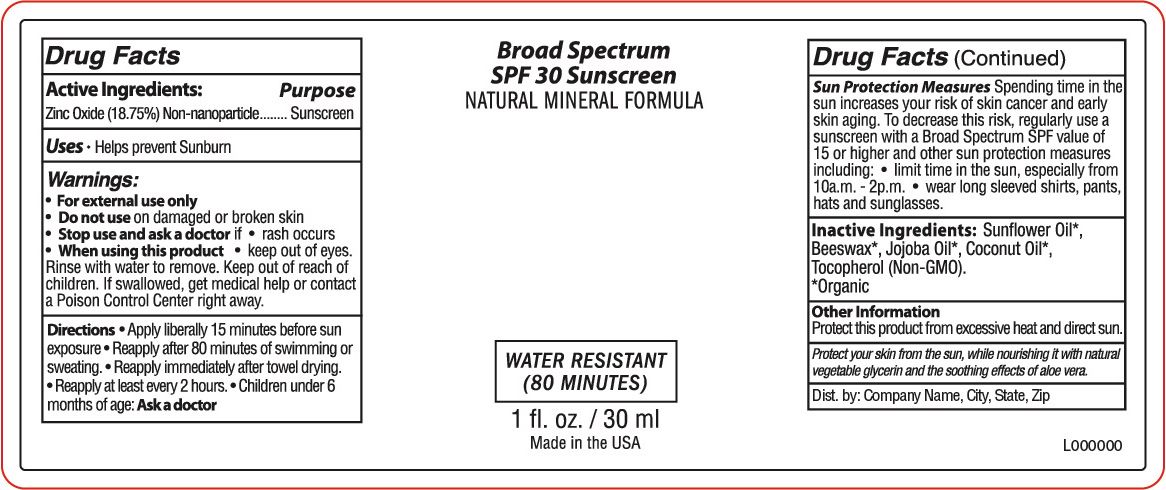 DRUG LABEL: Broad Spectrum SPF 30 Sunscreen
NDC: 65692-0567 | Form: LOTION
Manufacturer: Raining Rose
Category: otc | Type: HUMAN OTC DRUG LABEL
Date: 20231018

ACTIVE INGREDIENTS: ZINC OXIDE 5.625 g/30 mL
INACTIVE INGREDIENTS: WHITE WAX; SUNFLOWER OIL; COCONUT OIL; TOCOPHEROL; JOJOBA OIL

Broad Spectrum SPF 30 Mineral Sunscreen 1 fl oz

ACTIVE INGREDIENT

Zinc Oxide (18.75%)

PURPOSE

Sunscreen

INDICATIONS AND USAGE

Helps prevent Sunburn

WARNINGS

- For external use only
- Do not use on damaged or broken skin
- Stop use and ask a doctor if * rash occurs
- When using this product keep out of eyes. Rinse with water to remove.

Keep out of reach of children. If swallowed, get medical help or contact a Poison Control Center right away.

Directions

- Apply liberally 15 minutes before sun exposure
- Reapply after 80 minutes of swimming or sweating.
- Reapply immediately after towel drying.
- Reapply at least every 2 hours
- Children under 6 months of age: Ask a doctor

Sun Protection Measures Spending time in the sun increases your risk of skin cancer and early skin aging. To decrease this risk, regularly use a sunscreen with a Broad Spectrum SPF value of 15 or higher and other sunprotection measures including:

- limit time in the sun, especially from 10a.m.-2p.m.
- wear long sleeved shirts, pants, hats and sunglasses.

OTHER SAFETY INFORMATION

Protect this product from excessive heat and direct sun.

INACTIVE INGREDIENT

Inactive Ingredients: Sunflower Oil*, Beeswax*, Jojoba Oil*, Coconut Oil*, Tocopherol (Non-GMO). *Organic

DOSAGE AND ADMINISTRATION

Apply liberally 15 minutes before sun exposure

INDICATIONS AND USAGE

Helps prevent sunburn

PACKAGE LABEL

Broad Spectrum

SPF 30 Sunscreen

Natural Mineral Formula

Water Resistant

(80 minutes)

1 fl. oz. / 30 ml

Made in the USA